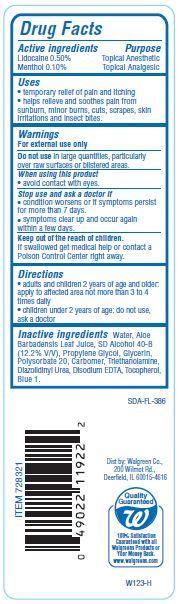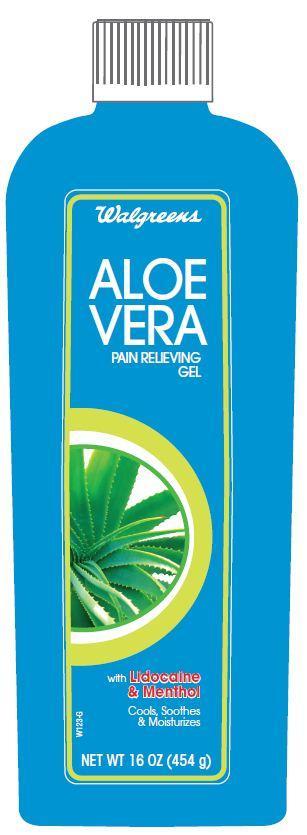 DRUG LABEL: Walgreens Aloe Vera
NDC: 0363-4003 | Form: GEL
Manufacturer: WALGREEN CO.
Category: otc | Type: HUMAN OTC DRUG LABEL
Date: 20121204

ACTIVE INGREDIENTS: LIDOCAINE 0.5 g/100 g; MENTHOL 0.10 g/100 g
INACTIVE INGREDIENTS: WATER; TROLAMINE; TOCOPHEROL; EDETATE DISODIUM; ALOE VERA LEAF; PROPYLENE GLYCOL; GLYCERIN; POLYSORBATE 20; DIAZOLIDINYL UREA; FD&C BLUE NO. 1

Drug Facts

Active ingredients

Lidocaine 0.50%
Menthol 0.10%

Purpose

Topical Anesthetic

Topical Analgesic

Uses

- temporary relief of pain and itching
- helps relieve and soothes pain from sunburn, minor burns, cuts, scrapes, skin irritations and insect bites.

Warnings

For external use only

Do not use In large quantities, particularly over raw surfaces or blistered areas.

When using this product

- avoid contact with eyes.

stop use and ask a doctor if

- conditions worsens or if symptoms persists for more than 7 days.
- symptoms clear up and occur again within a few days.

Keep out of the reach of children.

If swallowed get medical help or contact a Poison Control Center right away.

Directions

- adults and children 2 years of age and older.apply to affected area not more than 3 to 4 times daily
- children under 2 years of age: do not use, ask a doctor.

Inactive Ingredients

Water, Alcohol Denat., Propylene Glycol, Glycerin, Polysorbate 20, Carbomer, Triethanolamine, Diazolidinyl Urea, Aloe Barbadensis Leaf Juice, Tocopherol, Disodium EDTA, Blue 1.

Principal Display Panel

Walgreens
ALOE
VERA
PAIN RELIEVING
GEL
with Lidocaine
and Menthol
Cools Soothes
and Moisturizes
NET WT 16 OZ (454 g)